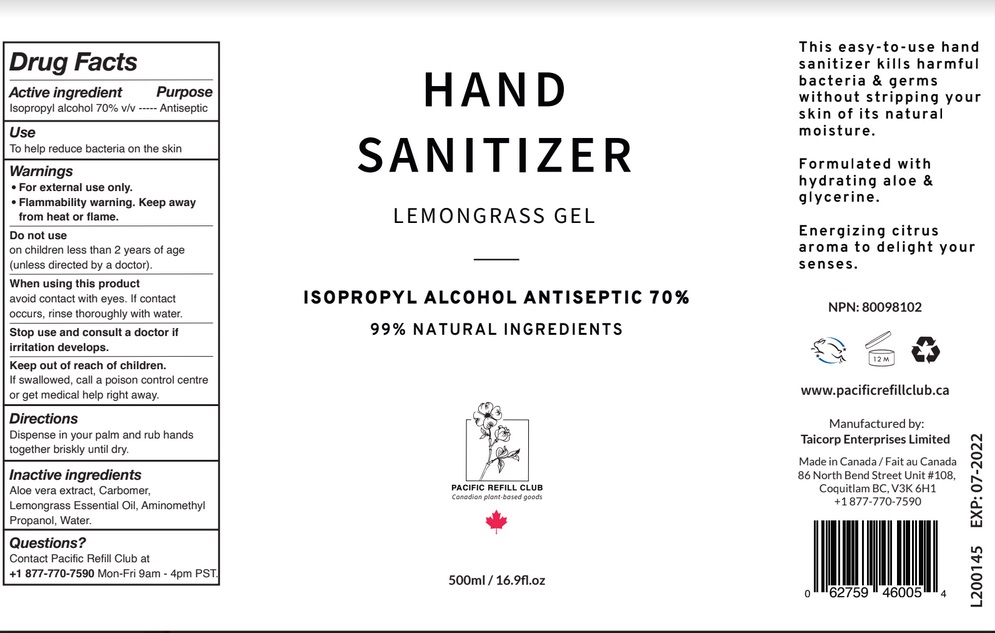 DRUG LABEL: Hand Sanitizer Lemongrass
NDC: 79883-001 | Form: LIQUID
Manufacturer: Taicorp Enterprises Limited
Category: otc | Type: HUMAN OTC DRUG LABEL
Date: 20200730

ACTIVE INGREDIENTS: ISOPROPYL ALCOHOL 70 mL/100 mL
INACTIVE INGREDIENTS: WATER; ALOE VERA LEAF; WEST INDIAN LEMONGRASS OIL; AMINOMETHYLPROPANOL; CARBOMER HOMOPOLYMER, UNSPECIFIED TYPE

Active Ingredient

Isopropyl alcohol 70% v/v

Purpose

Antiseptic

Use

To help reduce bacteria on the skin.

Warnings

For external use only.

Flammability warning: Keep away from heat or flame.

Do not use
on children less than 2 years of age (unless directed by a doctor).

When using this product avoid contact with eyes. If contact occurs, rinse thoroughly with water.

Stop use and consult a doctor if irritation develops.

Keep out of reach of children. If swallowed, get medical help or contact a Poison Control Center right away.

Directions

Dispense in your palm and rub hands together briskly until dry.

Inactive ingredients

Aloe vera extract, Carbomer, Lemongrass Essential Oil, Aminomethyl Propanol, Water.

Questions?
Contact Pacific Refill Club at
+1 877-770-7590 Mon-Fri 9am - 4pm PST.